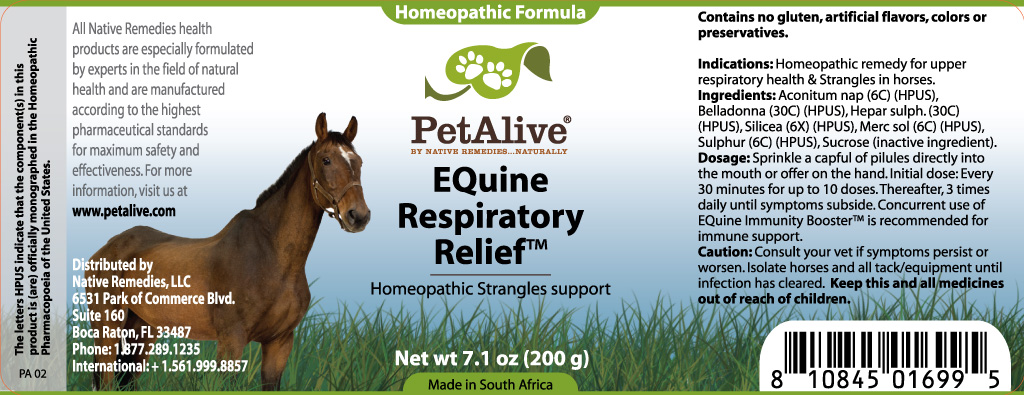 DRUG LABEL: Equine Respiratory Relief
NDC: 50048-072 | Form: GRANULE
Manufacturer: W LAST CC
Category: homeopathic | Type: OTC ANIMAL DRUG LABEL
Date: 20111122

ACTIVE INGREDIENTS: ACONITUM NAPELLUS 6 [hp_C]/33.3 mg; ATROPA BELLADONNA 30 [hp_C]/33.3 mg; CALCIUM SULFIDE 30 [hp_C]/33.3 mg; SILICON DIOXIDE 6 [hp_X]/33.3 mg; MERCURIUS SOLUBILIS 6 [hp_C]/33.3 mg; SULFUR 6 [hp_C]/33.3 mg
INACTIVE INGREDIENTS: SUCROSE

EQUINE RESPIRATORY RELIEF

PURPOSE

Homeopathic Strangles support

INDICATIONS AND USAGE

Indications: Homeopathic remedy for upper respiratory health and Strangles in horses.

DOSAGE AND ADMINISTRATION

Dosage: Sprinkle a capful of pilules directly into the mouth or offer on the hand. Initial dose: Every 30 minutes for up to 10 doses. Thereafter, 3 times daily until symptoms subside. Concurrent use of EQuine Immunity Booster™ is recommended for immune support.

GENERAL PRECAUTIONS

Caution: Consult your vet if symptoms persist or worsen. Isolate horses and all tack/equipment until infection has cleared. Keep this and all medicines out of reach of children.

ACTIVE INGREDIENT

Ingredients: Aconitum nap (6C) (HPUS), Belladonna (30C) (HPUS), Hepar sulph. (30C) (HPUS), Silicea (6X) (HPUS), Merc sol (6C) (HPUS), Sulphur (6C) (HPUS)

Sucrose (inactive ingredient).

WARNINGS

Contains no gluten, artificial flavors, colors or preservatives.

PATIENT COUNSELING INFORMATION

All Native Remedies health products are especially formulated by experts in the field of natural health and are manufactured according to the highest pharmaceutical standards for maximum safety and effectiveness. For more information, visit us at www.petalive.com

Distributed by

Native Remedies, LLC

6531 Park of Commerce Blvd.

Suite 160

Boca Raton, FL 33487

Phone: 1.877.289.1235

International: + 1.561.999.8857

The letters HPUS indicate that the component(s) in this product is (are) officially monographed in the Homeopathic Pharmacopoeia of the United States.

KEEP OUT OF REACH OF CHILDREN

Keep this and all medicines out of reach of children.